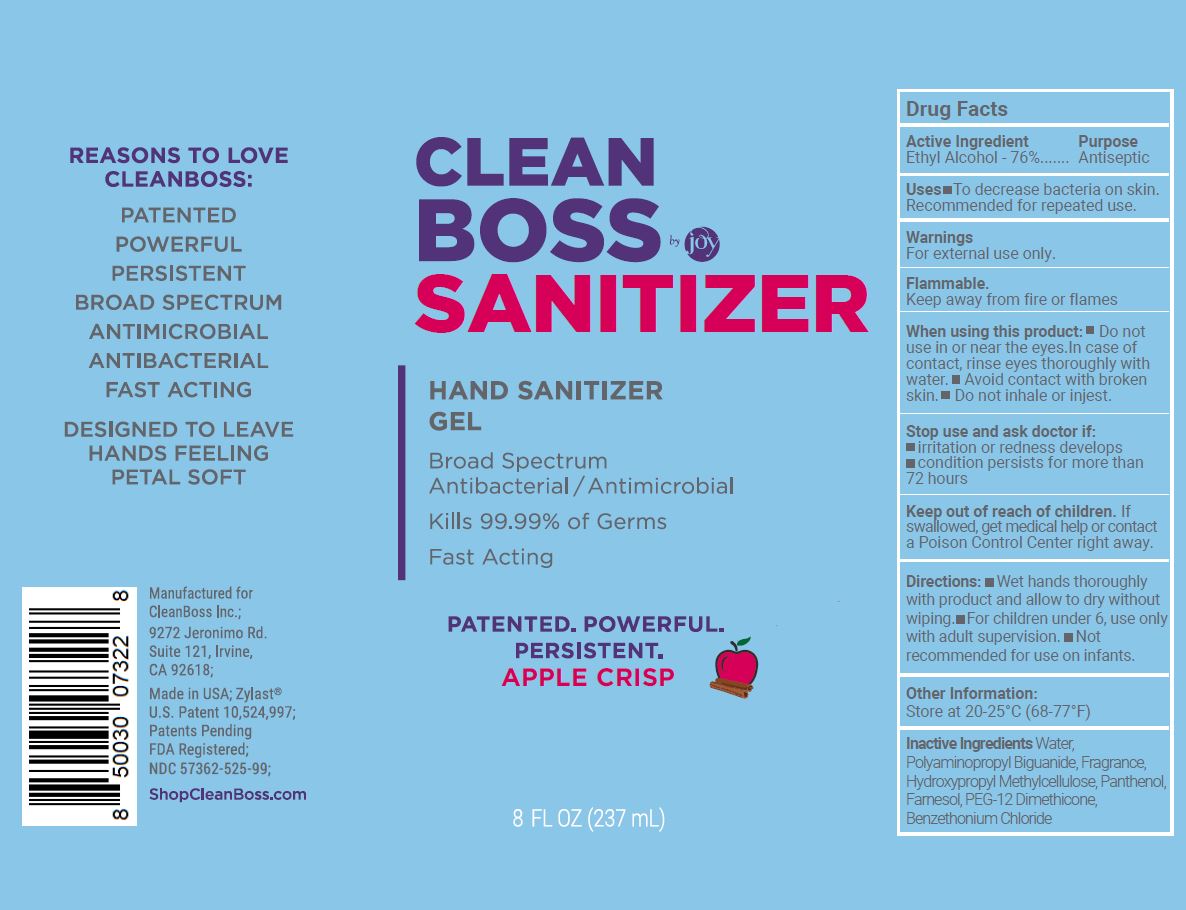 DRUG LABEL: CleanBoss Hand Sanitizing Gel
NDC: 57362-525 | Form: GEL
Manufacturer: Innovative Biodefense
Category: otc | Type: HUMAN OTC DRUG LABEL
Date: 20251002

ACTIVE INGREDIENTS: ALCOHOL 76 mL/100 mL
INACTIVE INGREDIENTS: WATER

CleanBoss
Apple Crisp
Hand Sanitizer Gel

ACTIVE INGREDIENT

Antiseptic 76%

INDICATIONS AND USAGE

- Handwash to decrease bacteria on the skin that potentially can cause disease.
- Recommended for repeated use.

WARNINGS

- For external use only
- Flammable.
- Keep away from fire or flames

- Do not use in or near the eyes. In case of contact, rinse eyes thoroughly with water.
- Avoid contact with broken skin.
- Do not inhale or ingest.

Stop use and ask a doctor if

- irritation or redness develops
- condition persists for more than 72 hours.

Keep out of reach of children.

If swallowed, get medical help or contact a Poison Control Center right away.

DOSAGE AND ADMINISTRATION

- Wet hands thoroughly with product and allow to dry without wiping.
- For children under 6, use only with adult supervision.
- Not recommended for use on infants.

OTHER SAFETY INFORMATION

Store at 20-25¹C (68-77ºF)

INACTIVE INGREDIENT

Benzethonium Chloride, Farnesol, Fragrance, Hydroxypropyl Methylcellulose, PEG-12 Dimethicone, Polyaminiopropyl Biguanide, Water

PURPOSE

Antiseptic